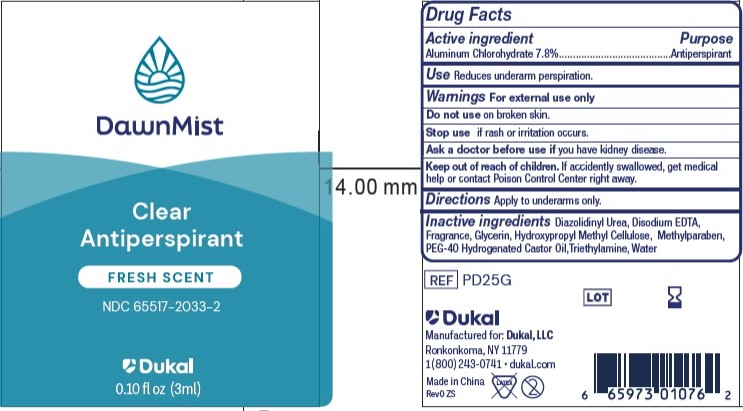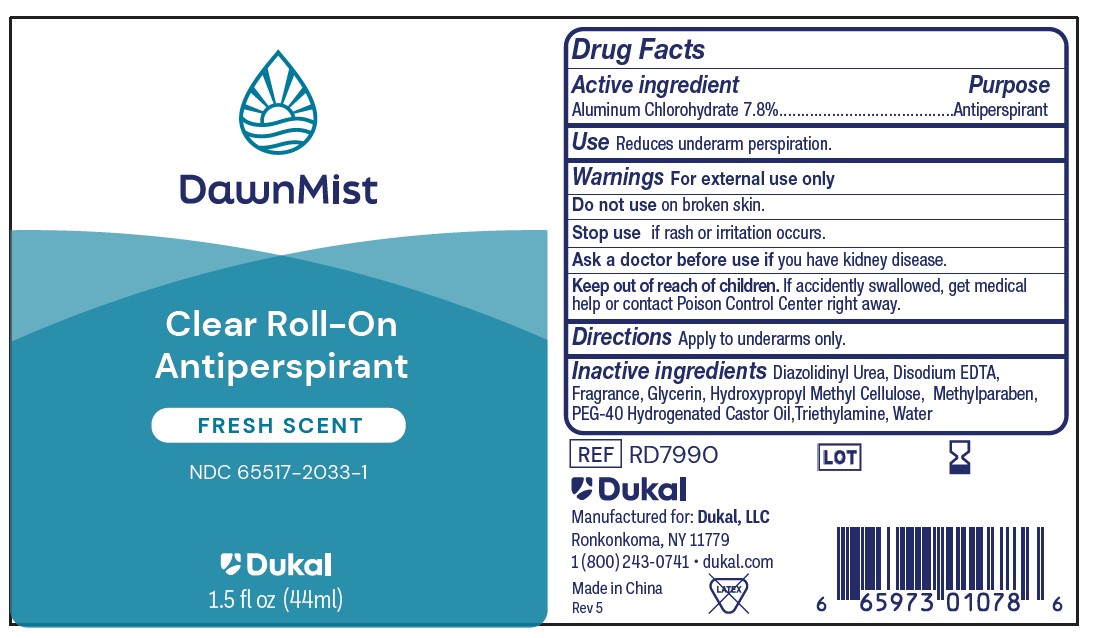 DRUG LABEL: DawnMist Antiperspirant
NDC: 65517-2033 | Form: LOTION
Manufacturer: Dukal LLC
Category: otc | Type: HUMAN OTC DRUG LABEL
Date: 20260217

ACTIVE INGREDIENTS: ALUMINUM CHLOROHYDRATE 78 mg/1 mL
INACTIVE INGREDIENTS: TRIETHYLAMINE; WATER; HYPROMELLOSES; POLYOXYL 40 HYDROGENATED CASTOR OIL; METHYLPARABEN; GLYCERIN; EDETATE DISODIUM; DIAZOLIDINYL UREA

DawnMist Antiperspirant 7.8% - Fresh Scent

Active Ingredient

Aluminum Chlorohydrate 7.8%

Purpose

Antiperspirant

Use

Reduces underarm perspiration

Warnings

For external use only.

Do not use on broken skin

Ask a doctor before use if you have kidney disease.

Keep out of reach of children. If accidently swallowed, get medical help or contact Poison Control Center right away.

Directions

Apply to underarms only.

Inactive ingredients

Diazolidinyl Urea, Disodium EDTA, Fragrance, Glycerin, Hydroxypropyl Methyl Cellulose, Methylparaben, PEG-40 Hydrogenated Castor Oil, Triethylamine, Water

PACKAGE LABEL

DawnMist

Clear Roll-On

Antiperspirant

Fresh Scent

NDC 65517-2033-1

Dukal

1.5FL.OZ. (44ml)

Principle Display Panel

DawnMist

Clear

Antiperspirant

Fresh Scent

NDC 65517-2033-2

Dukal

0.10 fl oz (3ml)